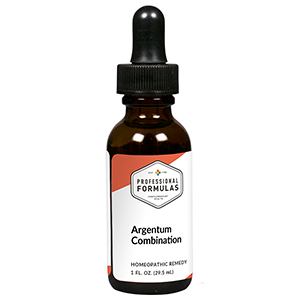 DRUG LABEL: Argentum Combination
NDC: 63083-9207 | Form: LIQUID
Manufacturer: Professional Complementary Health Formulas
Category: homeopathic | Type: HUMAN OTC DRUG LABEL
Date: 20190815

ACTIVE INGREDIENTS: AETHUSA CYNAPIUM WHOLE 4 [hp_X]/29.5 mL; IPECAC 4 [hp_X]/29.5 mL; ROBINIA PSEUDOACACIA BARK 4 [hp_X]/29.5 mL; SEMECARPUS ANACARDIUM JUICE 6 [hp_X]/29.5 mL; SILVER NITRATE 6 [hp_X]/29.5 mL; COLCHICUM AUTUMNALE BULB 6 [hp_X]/29.5 mL; STRYCHNOS IGNATII SEED 6 [hp_X]/29.5 mL; IODINE 6 [hp_X]/29.5 mL; LIQUID PETROLEUM 6 [hp_X]/29.5 mL; CLOSTRIDIUM BOTULINUM 12 [hp_X]/29.5 mL; LACHESIS MUTA VENOM 12 [hp_X]/29.5 mL; SALMONELLA ENTERICA ENTERICA SEROVAR TYPHI 12 [hp_X]/29.5 mL
INACTIVE INGREDIENTS: ALCOHOL; WATER

R207

ACTIVE INGREDIENTS

Aethusa cynapium 4X
Ipecacuanha 4X
Robinia pseudoacacia 4X
Anacardium orientale 6X
Argentum nitricum 6X
Colchicum autumnale 6X
Ignatia amara 6X
Iodium 6X
Petroleum 6X
Botulinum 12X
Lachesis mutus 12X
Salmonella 12X

QUESTIONS

Professional Formulas

PO Box 2034 Lake Oswego, OR 97035

INDICATIONS

For the temporary relief of stomach discomfort, heartburn, indigestion, nausea, or vomiting.*

PURPOSE

*Claims based on traditional homeopathic practice, not accepted medical evidence. Not FDA evaluated.

WARNINGS

In case of overdose, get medical help or contact a poison control center right away.

Keep out of the reach of children.

PREGNANCY OR BREAST FEEDING

If pregnant or breastfeeding, ask a healthcare professional before use.

DIRECTIONS

Place drops under tongue 30 minutes before/after meals. Adults and children 12 years and over: Take 10 drops up to 3 times per day. Consult a physician for use in children under 12 years of age.

OTHER INFORMATION

Tamper resistant. If seal is broken, do not use. After opening, close container tightly and store at room temperature away from heat.

INACTIVE INGREDIENTS

40% ethanol, purified water.

LABEL

Est 1985

Professional Formulas

Complementary Health

Argentum Combination

Homeopathic Remedy

1 FL. OZ. (29.5 mL)